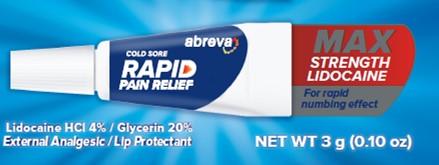 DRUG LABEL: ABREVA

NDC: 0135-0400 | Form: GEL
Manufacturer: Haleon US Holdings LLC
Category: otc | Type: HUMAN OTC DRUG LABEL
Date: 20240620

ACTIVE INGREDIENTS: GLYCERIN 200 mg/1 g; LIDOCAINE HYDROCHLORIDE 40 mg/1 g
INACTIVE INGREDIENTS: HYDROXYETHYL CELLULOSE, UNSPECIFIED; MENTHOL, UNSPECIFIED FORM; METHYLPARABEN; POLYSORBATE 80; PROPYLENE GLYCOL; PROPYLPARABEN; TRISODIUM CITRATE DIHYDRATE; WATER

Drug Facts

Active ingredients

Glycerin 20%

Lidocaine HCl 4%

Purposes

Lip Protectant

External Analgesic

Uses

- for the temporary relief of pain and itching associated with cold sores and fever blisters
- Relieves dryness and softens cold sores and fever blisters
- Softens crust (scabs) associated with cold sores and fever blisters

Warnings

For external use only

Do not use

- in large quantities, particularly over raw surfaces, or blistered areas

When using this product

1. do not get into eyes

Stop use and ask a doctor if

- condition worsens
- symptoms last more than 7 days or clear up and occur again within a few days

Keep out of reach of children.

If swallowed, get medical help or contact a Poison Control Center right away.

Directions

- push and turn cap to open, close tightly after use
- wash hands before and after applying
- adults and children 12 years of age and older: apply to affected area not more than 3 to 4 times daily
- children under 12 years: consult a doctor

Other information

- store at 20-25oC (68o-77oF)

Inactive ingredients

edetate disodium, hydroxyethyl cellulose, menthol, methylparaben, polysorbate 80, propylene glycol,

propylparaben, trisodium citrate dihydrate, water

Questions or comments?

1-877-709-3539

Additional Information

Retain outer carton for full product uses, directions and warnings.

Do not use if carton is broken or damaged.

CARTON Recycle

Principal Display Panel

abreva

RAPID

PAIN RELIEF

Cold Sore

MAX

STRENGTH

LIDOCAINE

For rapid numbing effect

Lidocaine HCl 4% / Glycerin 20%

External Analgesic / Lip Protectant

NET WT 3 g (0.10 oz)

PA 202119 – Front Panel